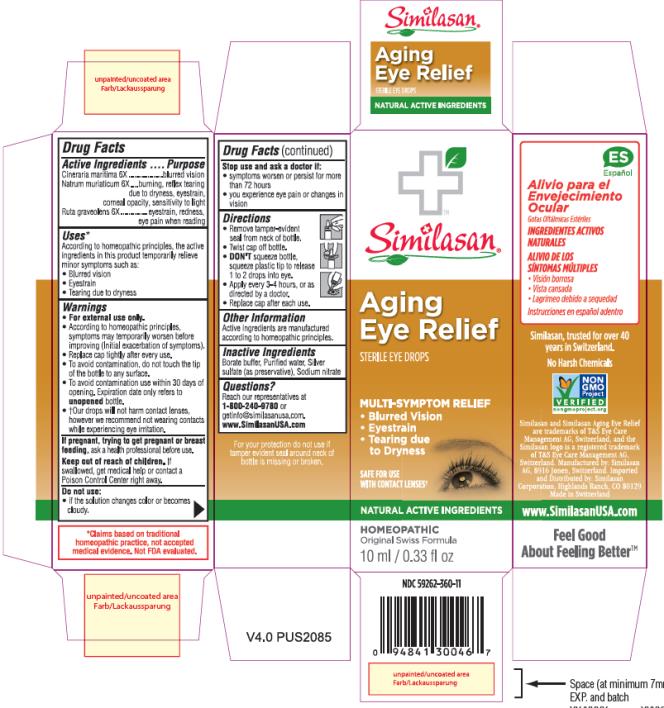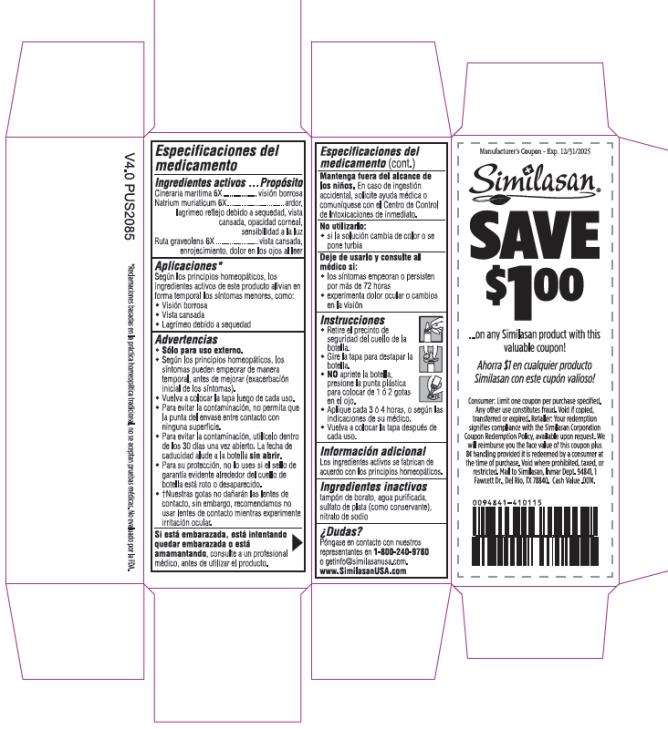 DRUG LABEL: Aging Eye Relief
NDC: 59262-360 | Form: SOLUTION/ DROPS
Manufacturer: Similasan Corporation
Category: homeopathic | Type: HUMAN OTC DRUG LABEL
Date: 20211028

ACTIVE INGREDIENTS: JACOBAEA MARITIMA 6 [hp_X]/10 mL; SODIUM CHLORIDE 6 [hp_X]/10 mL; RUTA GRAVEOLENS FLOWERING TOP 6 [hp_X]/10 mL
INACTIVE INGREDIENTS: BORIC ACID; WATER; SILVER SULFATE; SODIUM NITRATE

Aging Eye Relief

Active Ingredient

Cineraria maritima 6X

Purpose

Blurred vision

Active Ingredient

Natrium muriaticum 6X

Purpose

burning, reflex tearing due to dryness, eyestrain, corneal opacity, sensitivity to light

Active Ingredient

Ruta graveolens 6X

Purpose

eyestrain, rednesss, eye pain when reading

Uses:

According to homeopathic principles, the active ingredients in this medication help temporarily relieve minor symptoms such as:

- Blurred vision
- Eyestrain
- Tearing due to dryness

Warnings:

- For external use only.
- According to homeopathic principles, symptoms may temporarily worsen before improving (Initial exacerbation of symptoms).
- Replace cap tightly after every use.
- To avoid contamination, do not touch the tip of the container to any surface.
- To avoid contamination, use within 30 days of opening. Expiration date only refers to unopened bottle.
- †Our drops will not harm contact lenses, however we recommend not wearing contacts while experiencing eye irritation.

If pregnant, trying to get pregnant or breast feeding,

ask a health professional before use.

Keep out of reach of children.

If swallowed, get medical help or contact a Poison Control Center right away.

Do not use:

- if the solution changes color or becomes cloudy.

Stop use and ask a doctor if:

- symptoms worsen or persist for more than 72 hours
- you experience eye pain or changes in vision

Directions:

- Remove tamper-evident seal from neck of bottle.
- Twist cap off bottle.
- DON’T squeeze bottle, squeeze plastic tip to release 1 to 2 drops into eye.
- Apply every 3-4 hours, or as directed by a doctor.
- Replace cap after each use.

Other Information:

Active ingredients are manufactured according to homeopathic principles.

Inactive Ingredients:

Borate buffer, Purified water, Silver sulphate (as preservative), Sodium nitrate

Questions?

Reach our representatives at 1-800-240-9780 or getinfo@similasanusa.com.
www.SimilasanUSA.com

PRINCIPAL DISPLAY PANEL

NDC 59262-360-11
Similasan
Aging Eye Relief
STERILE EYE DROPS
10 ml / 0.33 fl oz